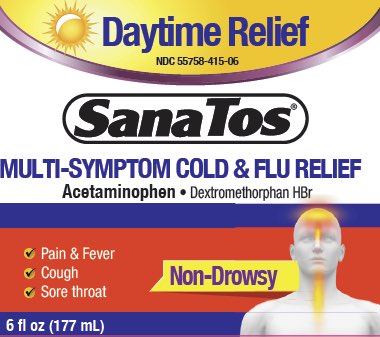 DRUG LABEL: Sanatos
NDC: 55758-415 | Form: LIQUID
Manufacturer: Pharmadel LLC
Category: otc | Type: HUMAN OTC DRUG LABEL
Date: 20231201

ACTIVE INGREDIENTS: DEXTROMETHORPHAN HYDROBROMIDE 20 mg/30 mL; ACETAMINOPHEN 650 mg/30 mL
INACTIVE INGREDIENTS: ANHYDROUS CITRIC ACID; WATER; FD&C YELLOW NO. 6; GLYCERIN; PROPYLENE GLYCOL; SODIUM BENZOATE; SUCRALOSE; SORBITOL SOLUTION; XANTHAN GUM; MENTHOL

Sanatos Daytime MS 6 (PLE)

Active ingredients & Purposes

PURPOSE

Active ingredients; (in each 30 mL) | Purposes
Acetaminophen 650 mg | Pain reliever/ fever reducer
Dextromethorphan HBr 20 mg | Cough suppressant

Uses

Temporarily relieves common cold/flu symptoms associted with

- minor aches & pains
- headache
- sore throat
- fever
- cough due to minor throat and bronchial irritation

Warnings

Liver warning: This product contains acetaminophen. Severe liver damage may occur if

- adults take more than 6 doses in 24 hours, which is the maxium daily amount
- child takes more than 4 doses in 24 hours
- taken with other drugs containing acetaminophen
- adult has 3 or more alcoholic drinks every day while using this product

Sore throat warning: If sore throat is severe, persists for more than 2 days, is accompanied or followed by fever, headache, rash, nausea, or vomiting, consult a doctor promptly.

Do not use

- if you are now taking a prescription monoamine oxidase inhibitor (MAOI) (certain drugs for depression, psychiatric or emotional conditions, or Parkinson's disease), or for 2 weeks after stopping the MAOI drug. If you do not know if your prescription drug contains an MAOI, ask a doctor or pharmacist before taking this product.
- with any other drug containing acetaminophen (prescription or nonprescription). If you are not sure whether a drug contains acetaminophen, ask a doctor or pharmacist.

Ask a doctor before use if user

- has a sodium restricted diet
- has liver disease
- hastrouble urinating due to enlarged prostate gland
- haspersistent or chronic cough such as occurs with smoking, asthma, or emphysema
- has a cough that occurs with too much phlegm (mucus)
- is a child with pain of arthritis

Ask a doctor or pharmacist before use if the user is

- taking the blood thinning drug warfarin

Stop use and ask a doctor if

- pain or cough gets worse or lasts more than 5 days (children) or 7 days (adults)
- fever gets worse or lasts more than 3 days
- redness or swelling is present
- new symptoms occur
- cough comes back or occurs with rash or headache that lasts.

These could be signs of a serious condition.

If pregnant or breast-feeding,

ask a health professional before use.

Keep out of reach of children.

In case of overdose, get medical help or contact a Poison Control Center right away. Prompt medical attention is critical for adults as well as for children even if you do not notice any signs or symptoms.

Directions

- use only dosing cup provided
- shake well before use
- if you are taking other cold/flu products, read complete labeling before dosing

adults & children 12 years & over | 30 mL every 4 hours, do not exceed (child) 4 doses and (adult) 6 doses per 24 hours
children under 12 years of age | do not use

Other information

- sodium content per tablespoon: 10 mg
- store at room temperature

TAMPER EVIDENT: Do not use if imprinted band is missing or broken.

Inactive ingredients

citric acid anhydrous, FD&C yellow #6, flavor, glycerin, menthol, propylene glycol, sodium benzoate, sorbitol solution, sodium citrate, sucralose, xanthan gum, water

Questions?

+1-866-359-3478 (M-F) 9AM – 5PM EST or www.pharmadel.com

Distributed by:

Pharmadel LLC

New Castle, DE 19720

www.pharmadel.com

Facebook/PHARMADELUSA